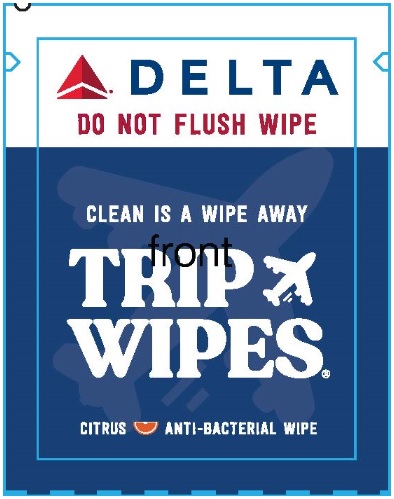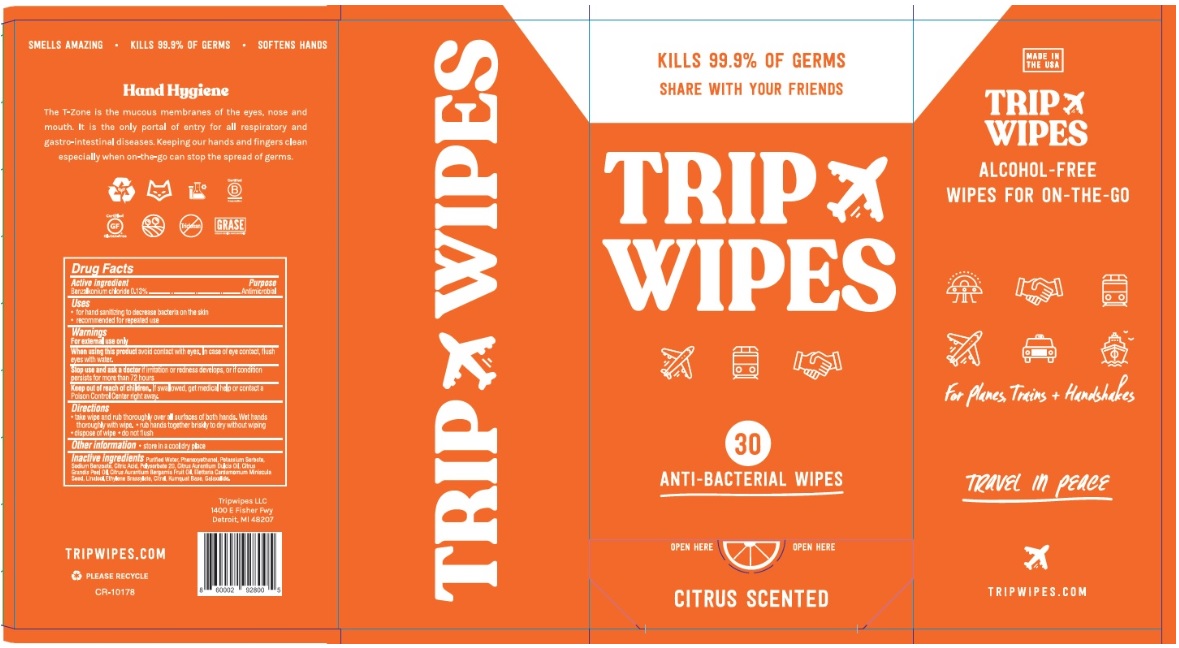 DRUG LABEL: Trip Wipes
NDC: 73030-020 | Form: SWAB
Manufacturer: DETROIT WICK
Category: otc | Type: HUMAN OTC DRUG LABEL
Date: 20241206

ACTIVE INGREDIENTS: BENZALKONIUM CHLORIDE 0.13 g/100 g
INACTIVE INGREDIENTS: WATER; PHENOXYETHANOL; POTASSIUM SORBATE; SODIUM BENZOATE; CITRIC ACID MONOHYDRATE; POLYSORBATE 20; ORANGE OIL; CITRUS MAXIMA FRUIT RIND OIL; BERGAMOT OIL; LINALOOL, (+/-)-; ETHYLENE BRASSYLATE; CITRAL; CITRUS JAPONICA FRUIT; HEXAMETHYLINDANOPYRAN

Drug Facts

Active ingredient

Benzalkonium chloride 0.13%

Purpose

Antimicrobial

Uses

- For hand sanitizing to decrease bacteria on the skin
- Recommended for repeated use

Warnings

For external use only

When using this product

avoid contact with eyes. In case of eye contact, flush eyes with water.

Stop use and ask a doctor

If irritation or redness develops, or if condition persists for more than 72 hours.

Keep out of reach of children

If swallowed, get medical help or contact a Poison Control Center right away.

Directions

- take wipe and rub thoroughly over all surfaces of both hands. Wet hands thoroughly with wipe
- rub hands together briskly to dry without wiping
- dispose of wipe
- do not flush

Other information

Store in a cool dry place

Inactive ingredients

Purified Water, Phenoxyethanol, Potassium Sorbate, Sodium Benzoate, Citric Acid, Polysorbate 20, Citrus Aurantium Dulcis Oil, Citrus Grandis Peel Oil, Citrus Aurantium Bergamia Fruit Oil, Elettaria Cardamomum Miniscula Seed, Linolool, Ehylene Brassylate, Citral, Kumquat Base, Galaxolide

Principal Display Panel

NDC 73030-020-02

DO NOT FLUSH

CLEAN IS A WIPE AWAY

TRIP WIPES

CITRUS ANTI-BACTERIAL WIPE

1 INDIVIDUAL WIPE

NDC 73030-020-01

MADE IN THE USA

ALCOHOL-FREE WIPES FOR ON-THE-GO

For Planes, Trains +

Handshakes

TRAVEL IN PEACE

KILLS 99.9% OF GERMS

SMELLS AMAZING

SOFTENS HANDS

SHARE WITH YOU FRIENDS

30 ANTIBACTERIAL WIPES

CITRUS SCENTED

TRIPWIPES.COM